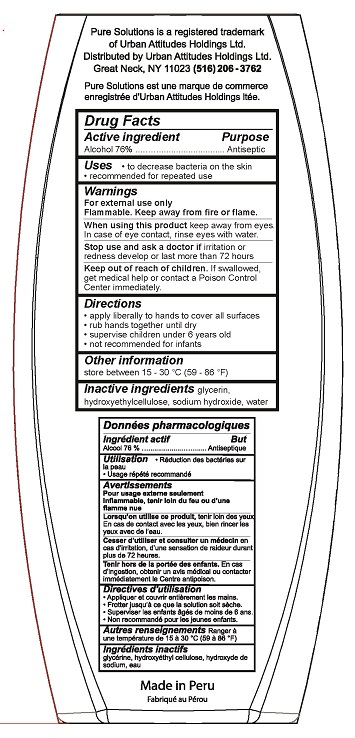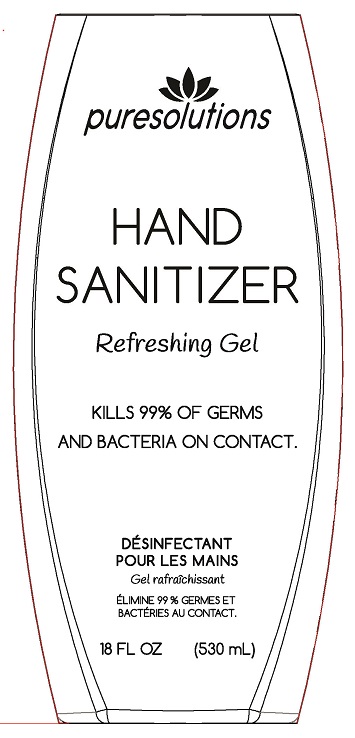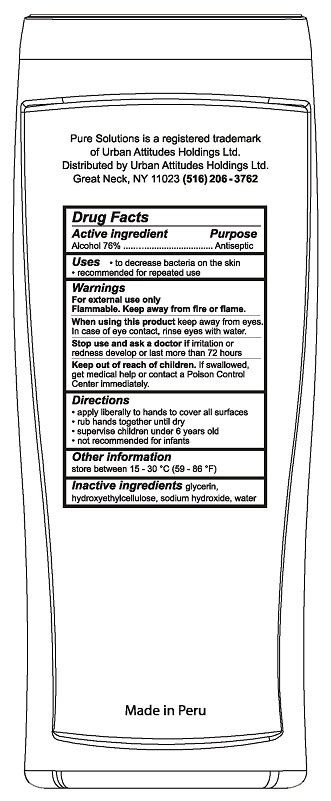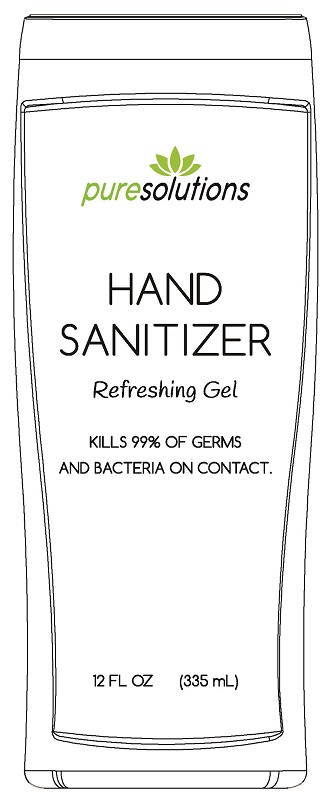 DRUG LABEL: Pure Solutions Hand Sanitizer
NDC: 77185-001 | Form: LIQUID
Manufacturer: Urban Attitudes Holdings Ltd
Category: otc | Type: HUMAN OTC DRUG LABEL
Date: 20200502

ACTIVE INGREDIENTS: ALCOHOL 76 mL/100 mL
INACTIVE INGREDIENTS: SODIUM HYDROXIDE; HYDROXYETHYL CELLULOSE, UNSPECIFIED; WATER; GLYCERIN

Pure Solutions Hand Sanitizer

Drug Facts

Active ingredient

Alcohol 76%

Purpose
Antiseptic

Uses

- to decrease bacteria on the skin
- recommended for repeated use

Warnings
For external use only.
Flammable. Keep away from heat or flame.

When using this product keep away from eyes. In case of eye contact, rinse eyes with water.

Stop use and ask a doctor if irritation or redness develop or last more than 72 hours.

Keep out of reach of children. If swallowed, get medical help or contact a Poison Control Center immediately.

Directions

- apply liberally to hands to cover all surfaces
- rub hands together until dry
- supervise children under 6 years old
- not recommended for infants

Other information

store between 15-30°C (59-86°F)

Inactive ingredients

glycerin, hydroxyethylcellulose, sodium hydroxide, water

Pure Solutions is a registered trademark of Urban Attitudes Holdings Ltd.

Distributed by:

Urban Attititudes Holdings Ltd.

Great Neck, NY 11023

(516) 206-3672

Made in Peru

PACKAGE LABEL

puresolutions

HAND SANITIZER

Refreshing Gel

KILLS 99% GO GERMS AND BACTERIA ON CONTACT.

18 FL OZ (530 mL)

PACKAGE LABEL

puresolutions

HAND SANITIZER

Refreshing Gel

KILLS 99% OF GERMS AND BACTERIA ON CONTACT.

12 FL OZ (355 mL)